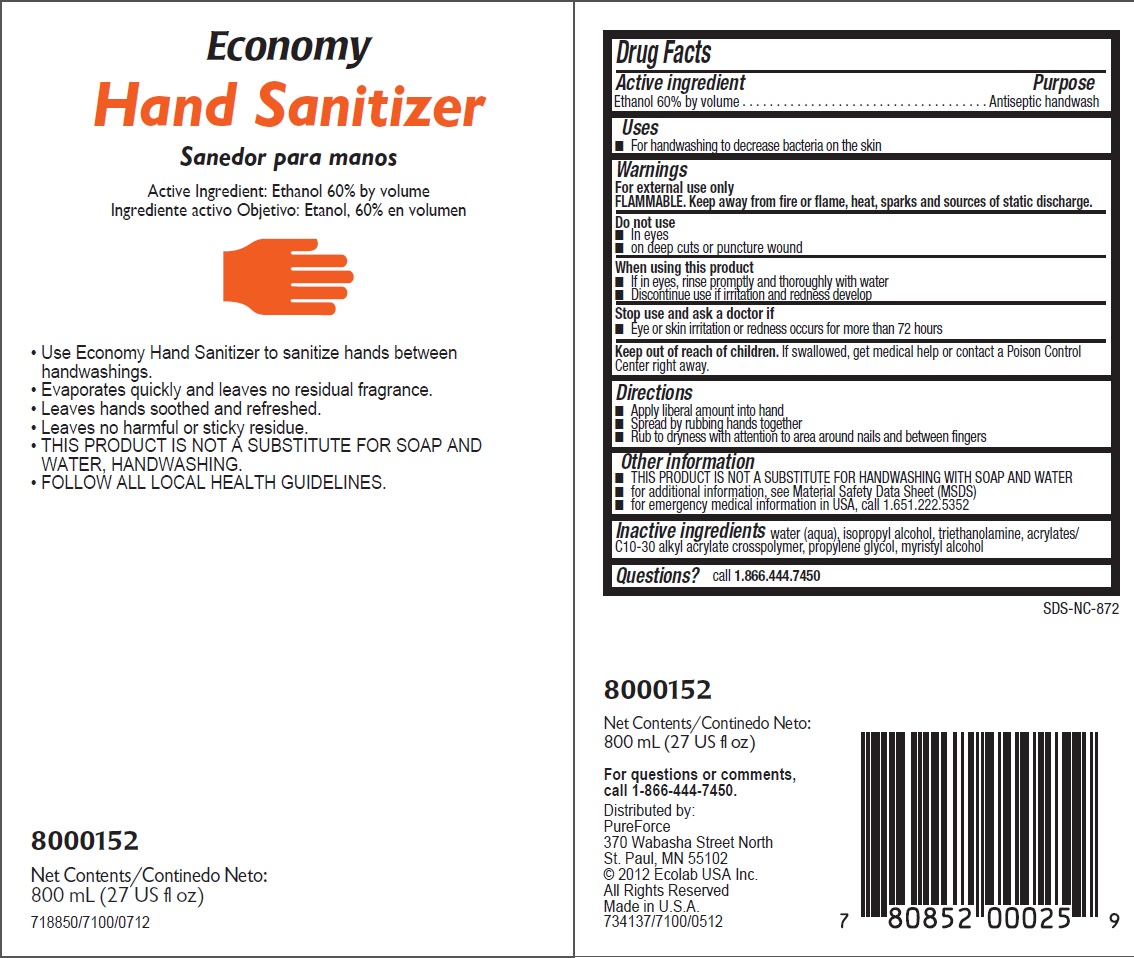 DRUG LABEL: PureForce
NDC: 47593-498 | Form: SOLUTION
Manufacturer: Ecolab Inc.
Category: otc | Type: HUMAN OTC DRUG LABEL
Date: 20251230

ACTIVE INGREDIENTS: ALCOHOL 534 mg/1 mL
INACTIVE INGREDIENTS: WATER; ISOPROPYL ALCOHOL; TROLAMINE; POLYACRYLAMIDE (10000 MW); PROPYLENE GLYCOL; MYRISTYL ALCOHOL

Drug Facts

Active ingredient

Ethanol 60% by volume

Purpose

Antiseptic handwash

Uses

- For handwashing to decrease bacteria on the skin

Warnings

For external use only

FLAMMABLE. Keep away from fire or flame, heat , sparks and sources of static discharge.

Do not use

- In eyes
- on deep cuts or puncture wound

When using this product

- If in eyes, rinse thoroughly with water
- Discontinue use if irritation and redness develop

Stop use and ask a doctor if

- Eye or skin irritation or redness occurs for more than 72 hours

Keep out of reach of children. If swallowed, get medical help or contact a Poison Control Center right away.

Directions

- Apply liberal amount into hand
- Spread by rubbing hands together
- Rub to dryness with attention to area around nails and between fingers

Other information

- THIS PRODUCT IS NOT A SUBSTITUTE FOR HANDWASHING WITH SOAP AND WATER
- for additional information, see Material Safety Data Sheet (MSDS)
- for emergency medical information in USA, call 1.651.222.5352

INACTIVE INGREDIENT

Inactive ingredients water (aqua), isopropyl alcohol, triethanolamine, acrylates/C10-30 alkyl acrylate crosspolymer, propylene glycol, myristyl alcohol

Questions? call 1.866.444.7450

Principal Display Panel and Representative Label

Economy

Hand Sanitizer

Active Ingredient: Ethanol 60% by volume

- Use Economy Hand Sanitizer to sanitize hands between handwashings.
- Evaporates quickly and leaves no residual fragrance.
- Leaves hands soothed and refreshed.
- Leaves no harmful or sticky residue.
- THIS PRODUCT IS NOT A SUBSTITUTE FOR SOAP AND WATER, HANDWASHING.
- FOLLOW ALL LOCAL HEALTH GUIDELINES.

8000152

Net Contents: 800 mL (27 US fl oz)

718850/7100/0712